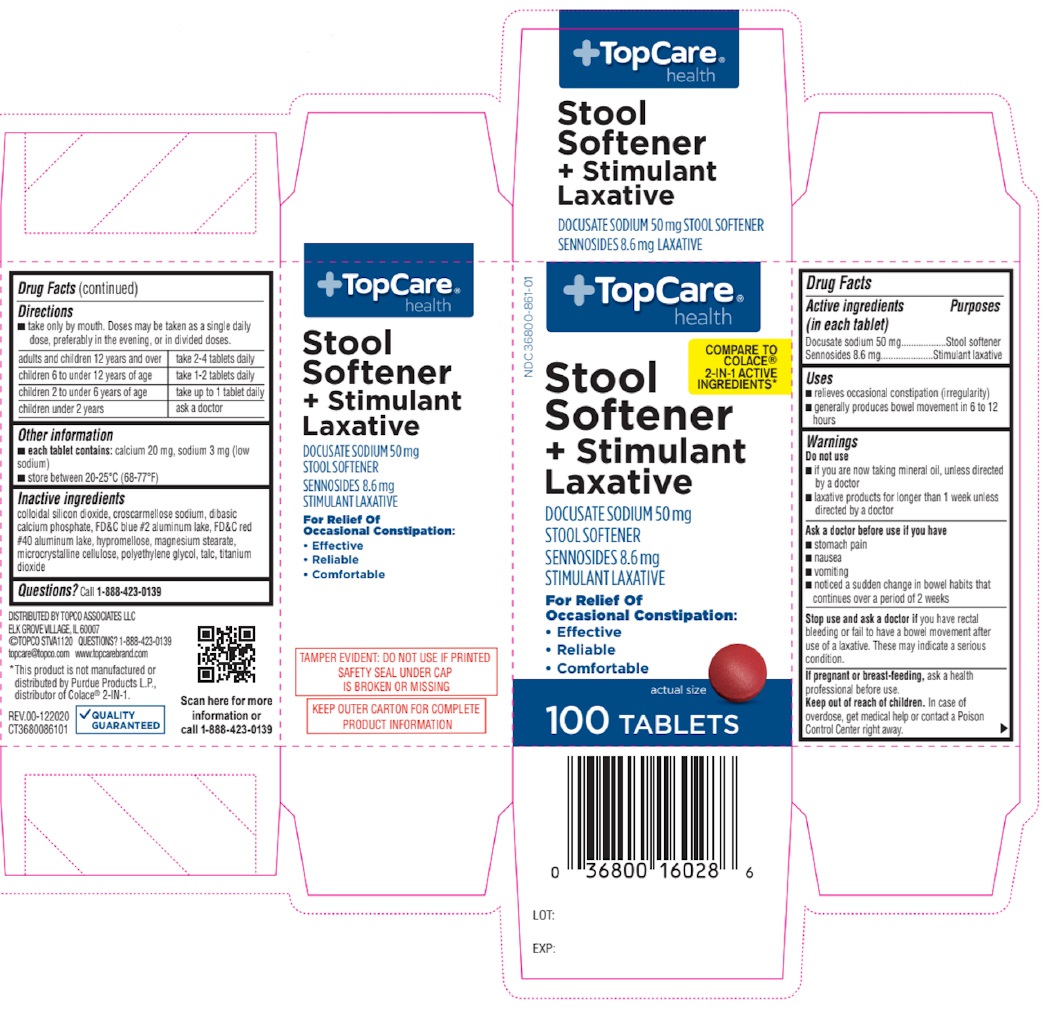 DRUG LABEL: Laxative Docusate Sodium with Senna
NDC: 36800-861 | Form: TABLET, COATED
Manufacturer: TOPCO ASSOCIATES LLC
Category: otc | Type: HUMAN OTC DRUG LABEL
Date: 20250101

ACTIVE INGREDIENTS: DOCUSATE SODIUM 50 mg/1 1; SENNOSIDES 8.6 mg/1 1
INACTIVE INGREDIENTS: SILICON DIOXIDE; CROSCARMELLOSE SODIUM; ANHYDROUS DIBASIC CALCIUM PHOSPHATE; FD&C BLUE NO. 2 ALUMINUM LAKE; FD&C RED NO. 40 ALUMINUM LAKE; HYPROMELLOSE, UNSPECIFIED; MAGNESIUM STEARATE; MICROCRYSTALLINE CELLULOSE; POLYETHYLENE GLYCOL, UNSPECIFIED; TALC; TITANIUM DIOXIDE

Laxative Docusate Sodium with Senna

Active ingredients (in each tablet)

Docusate sodium 50 mg
Sennosides 8.6 mg

Purposes

Stool softener
Stimulant laxative

Uses

• relieves occasional constipation (irregularity)
• generally produces bowel movement in 6 to 12 hours

Warnings

Do not use
• if you are now taking mineral oil, unless directed by a doctor
• laxative products for longer than 1 week unless directed by a doctor

Ask a doctor before use if you have
• stomach pain
• nausea
• vomiting
• noticed a sudden change in bowel habits that continues over a period of 2 weeks

Stop use and ask a doctor if you have rectal bleeding or fail to have a bowel movement after use of a laxative. These may indicate a serious condition.

If pregnant or breast-feeding, ask a health professional before use.

Keep out of reach of children. In case of overdose, get medical help or contact a Poison Control Center right away.

Directions

• take only by mouth. Doses may be taken as a single daily dose, preferably in the evening, or in divided doses.

adults and children 12 years and over | take 2-4 tablets daily
children 6 to under 12 years of age | take 1-2 tablets daily
children 2 to under 6 years of age | take up to 1 tablet daily
children under 2 years | ask a doctor

Other information

• each tablet contains: calcium 20 mg, sodium 3 mg (low sodium)
• store between 20-25°C (68-77°F)

Inactive ingredients

colloidal silicon dioxide, croscarmellose sodium, dibasic calcium phosphate, FD&C blue #2 aluminum lake, FD&C red #40 aluminum lake, hypromellose, magnesium stearate, microcrystalline cellulose, polyethylene glycol, talc, titanium dioxide

Questions?

Call 1-888-423-0139

+TopCare® health

COMPARE TO COLACE® 2-IN-1 ACTIVE INGREDIENTS*

Stool Softener + Stimulant Laxative

For Relief Of Occasional Constipation:
• Effective
• Reliable
• Comfortable

DISTRIBUTED BY TOPCO ASSOCIATES LLC

ELK GROVE VILLAGE, IL 60007

©TOPCO STVA1120

topcare@topco.com

www.topcarebrand.com

*This product is not manufactured or distributed by Purdue Products L.P., distributor of Colace® 2-IN-1.

TAMPER EVIDENT: DO NOT USE IF PRINTED SAFETY SEAL UNDER CAP IS BROKEN OR MISSING

KEEP OUTER CARTON FOR COMPLETE PRODUCT INFORMATION